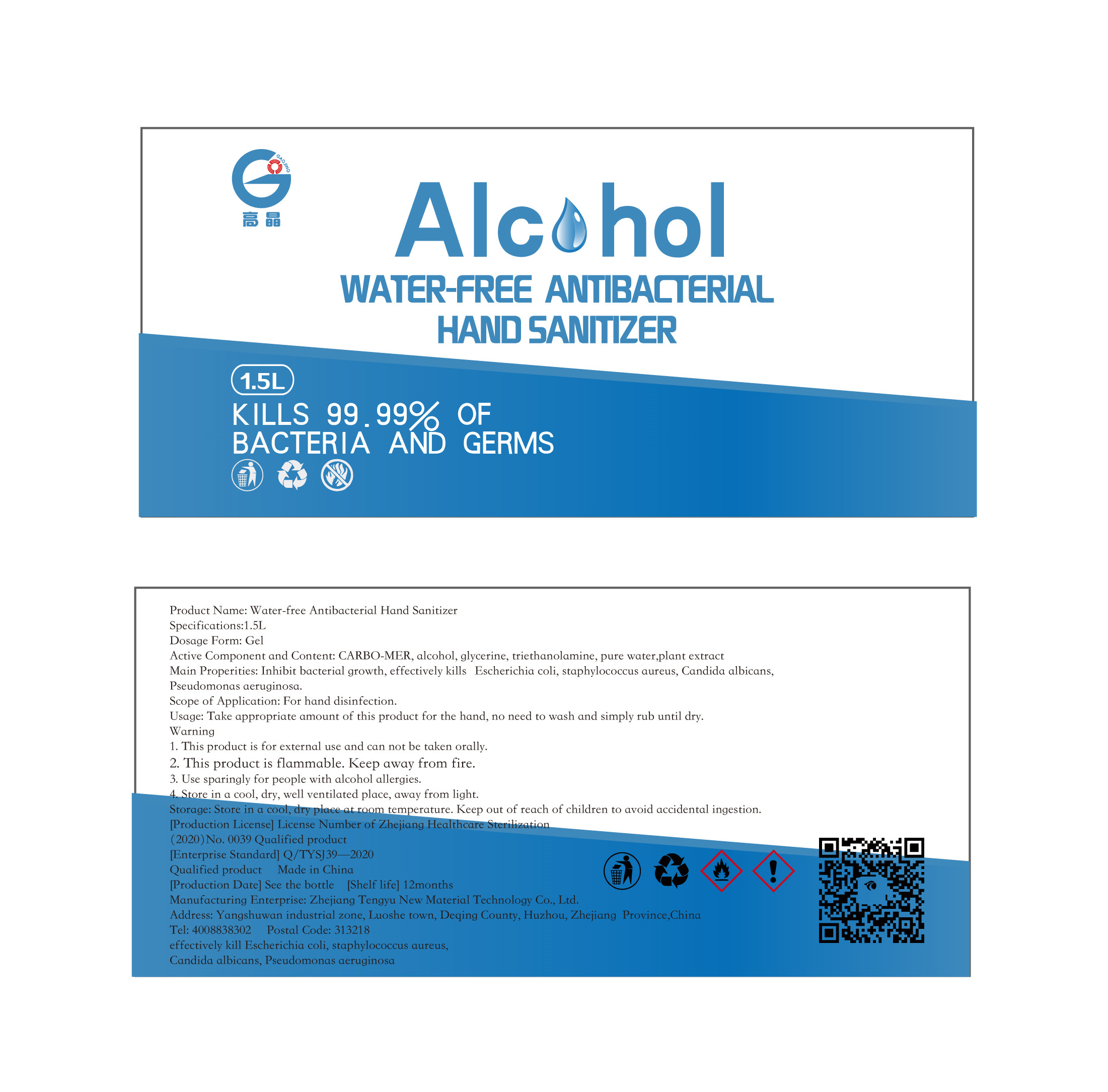 DRUG LABEL: Water-free Antibacterial  Hand Sanitizer
NDC: 54983-004 | Form: GEL
Manufacturer: Zhejiang Tengyu New Material Technology Co., Ltd.
Category: otc | Type: HUMAN OTC DRUG LABEL
Date: 20220421

ACTIVE INGREDIENTS: ALCOHOL 1125 mL/1500 mL
INACTIVE INGREDIENTS: TROLAMINE; WATER; GLYCERIN; CARBOMER HOMOPOLYMER, UNSPECIFIED TYPE

DOSAGE AND ADMINISTRATION

Store in a cool, dry, well ventilated place, away from light.

INACTIVE INGREDIENT

Pure Water

plant extract

Gycerinum

Triethanolamine

Carbomer

INDICATIONS AND USAGE

Take appropriate amount of this product for the hand,no need to wash and simply rub until dry.

ACTIVE INGREDIENT

Ethyl alcohol

keep out of reach of children

PURPOSE

Disinfection
Sterilization
No Rinseing

WARNINGS

1. This product is for external use and can not be taken orally.
2. 'This product is flammable. Keep away from fire.
3. Use sparingly for people with alcohol allergies.
4. Store in a cool, dry, well ventilated place, away from light.